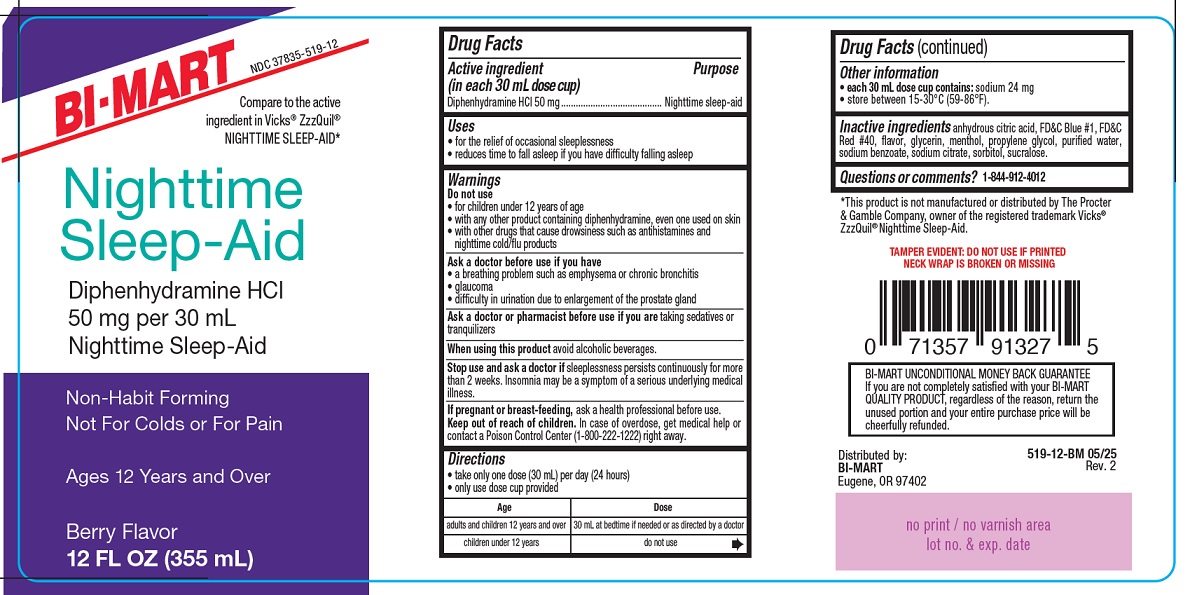 DRUG LABEL: Diphenhydramine HCl
NDC: 37835-519 | Form: LIQUID
Manufacturer: BI-MART
Category: otc | Type: HUMAN OTC DRUG LABEL
Date: 20250520

ACTIVE INGREDIENTS: DIPHENHYDRAMINE HCL 50 mg/30 mL
INACTIVE INGREDIENTS: SUCRALOSE; SORBITOL SOLUTION 70%; WATER; PROPYLENE GLYCOL; SODIUM BENZOATE; FD&C RED NO. 40; SODIUM CITRATE; CITRIC ACID; FD&C BLUE NO. 1; GLYCERIN; MENTHOL

Nighttime Sleep-Aid

Drug Facts

Active ingredient (in each 30 mL dose cup)

Diphenhydramine HCl 50mg

Purpose

Nightime sleep-aid

Uses

• for the relief of occasional sleeplessness
• reduces time to fall asleep if you have difficulty falling asleep

Warnings

Do not use

• for children under 12 years of age
• with any other product containing diphenhydramine, even one used on skin
• with other drugs that cause drowsiness such as antihistamines and nighttime cold/flu products

Ask a doctor before use if you have

• a breathing problem such as emphysema or chronic bronchitis
• glaucoma
• difficulty in urination due to enlargement of the prostate gland

Ask a doctor or pharmacist before use if you are

taking sedatives or tranquilizers

When using this product

avoid alcoholic beverages

Stop use and ask a doctor if

sleeplessness persists continuosly for more than 2 weeks. Insomnia may be a symptom of serious underlying medical ilness.

If pregnant or breast-feeding,

ask a health professional before use.

Keep out of the reach of children.

In case of overdose, get medical help or contact a Poison Control Center (1-800-222-1222) right away.

Directions

• take only one dose (30 mL) per day (24 hours)
• only use dose cup provided

Age | Dose
adults and children 12 years and over | 30 mL at bedtime if needed or as directed by a doctor
children under 12 years | do not use

Other information

• each 30 mL dose cup contains:sodium 24 mg
• store between 15-30°C (59-86°F).

Inactive ingredients

anhydrous citric acid, FD&C Blue #1, FD&C Red #40, flavor, glycerin, menthol, propylene glycol, purified water, sodium benzoate, sodium citrate, sorbitol, sucralose.

Questions or comments?

1-844-912-4012